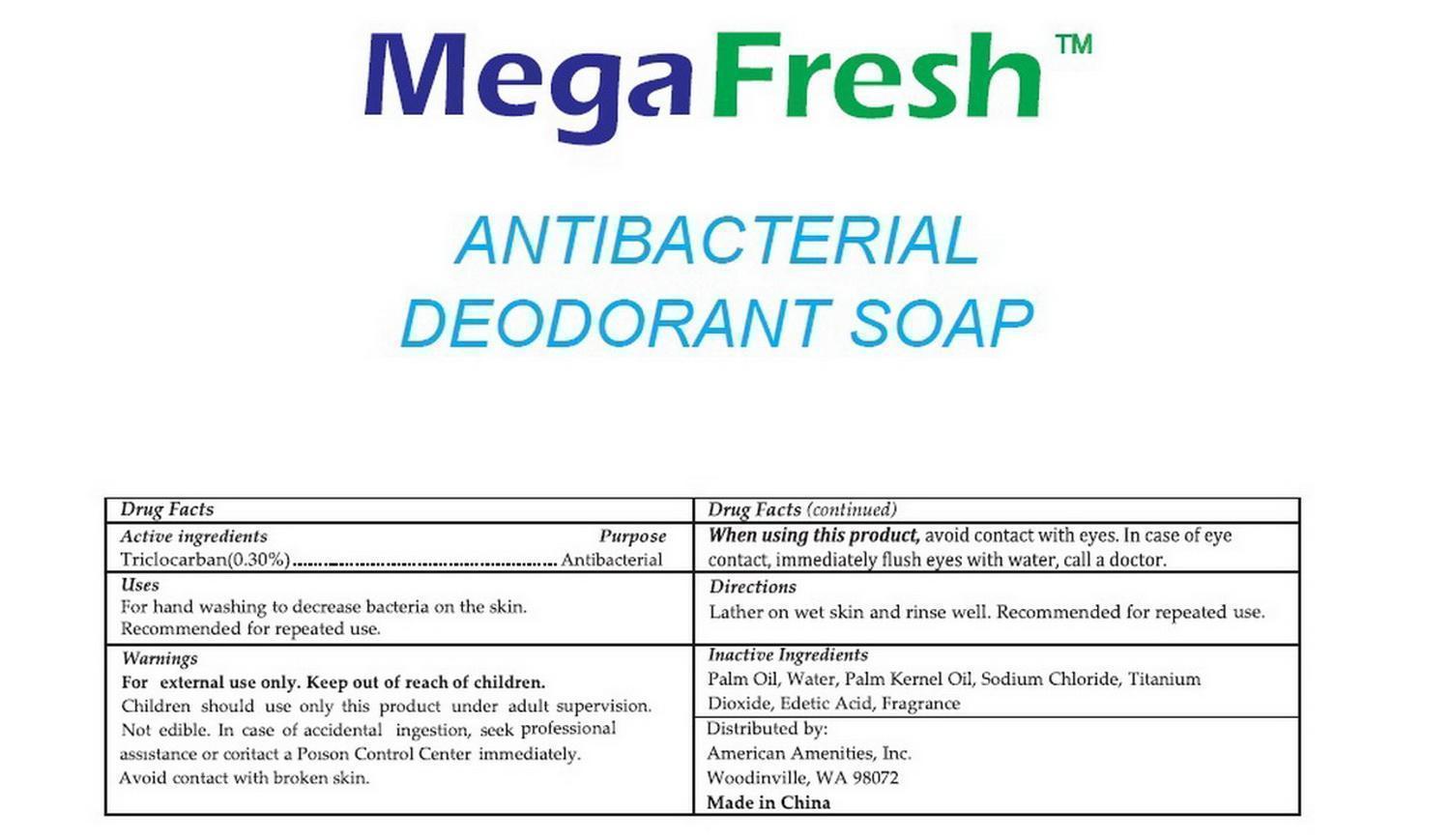 DRUG LABEL: MegaFresh Antibacterial Deodorant
NDC: 54157-101 | Form: SOAP
Manufacturer: American Amenities, Inc.
Category: otc | Type: HUMAN OTC DRUG LABEL
Date: 20150530

ACTIVE INGREDIENTS: TRICLOCARBAN 0.3 g/100 g
INACTIVE INGREDIENTS: WATER; PALM OIL; PALM KERNEL OIL; SODIUM CHLORIDE; TITANIUM DIOXIDE; EDETIC ACID

Active Ingredient: Triclocarban (0.3%)

Purpose: Antibacterial

INDICATIONS AND USAGE

Uses: For hand washing to decrease bacteria on the skin. Recommended for repeated use.

WARNINGS

For external use only. Keep out of reach of children

KEEP OUT OF REACH OF CHILDREN

Children should use only this product under adults supervision. Not edible. In case of accidental ingestion, seek professional assistance or contact a Poison Control Center immediately. Avoid contact with broken skin.

When using this product, avoid contact with eyes. In case of eye contact, immediately flush eyes with water, call a doctor

DOSAGE AND ADMINISTRATION

Lather on wet skin and rinse well. Recommended for repeated use

INACTIVE INGREDIENT

Palm Oil, Water, Palm Kernel Oil, Sodium Chloride, Titanium Dioxide, Edetic Acid, Fragrance